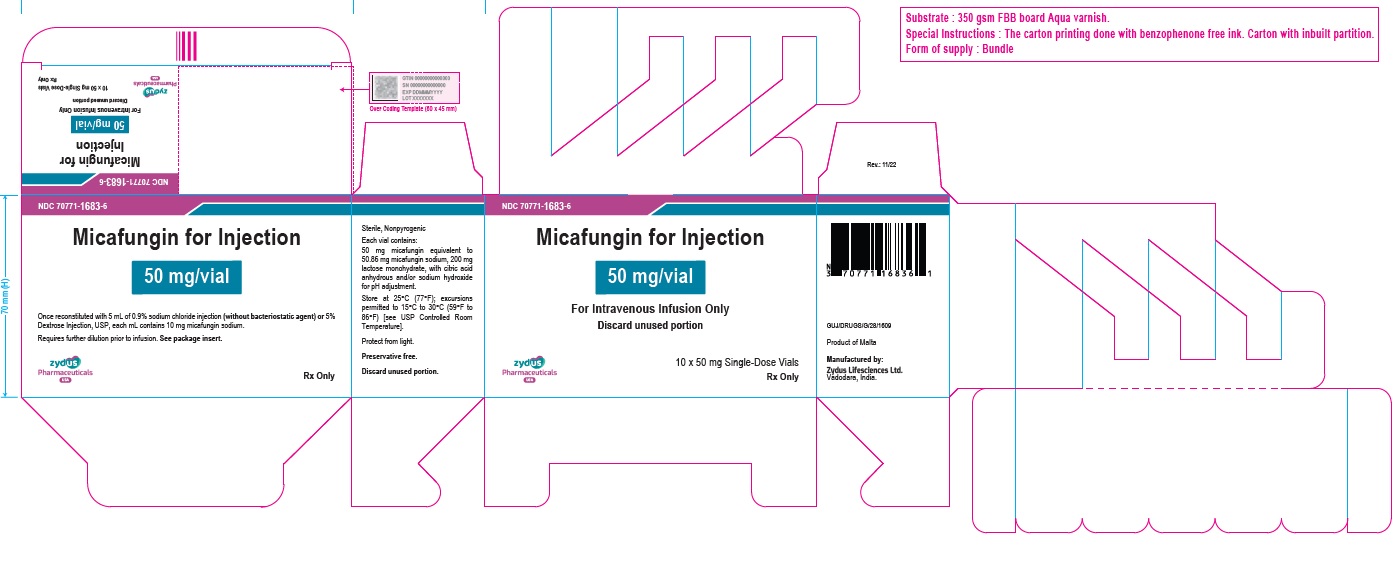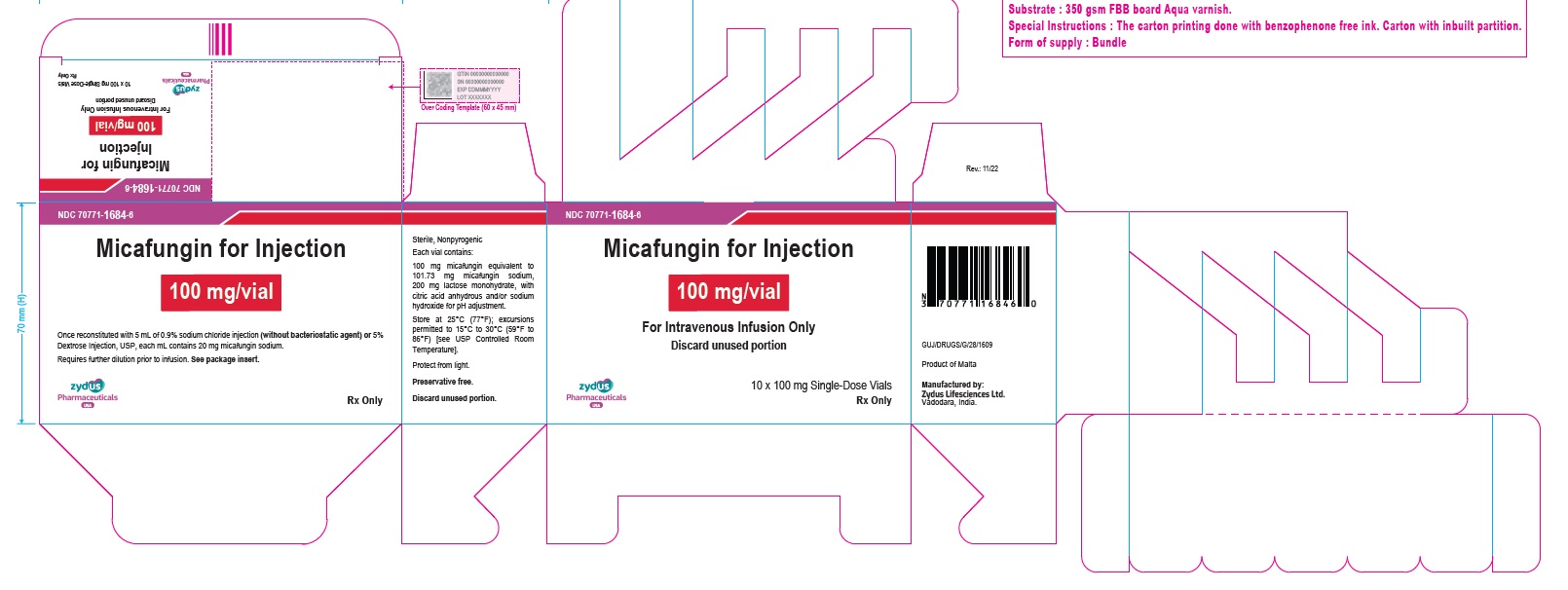 DRUG LABEL: Micafungin
NDC: 70771-1683 | Form: INJECTION, POWDER, LYOPHILIZED, FOR SOLUTION
Manufacturer: Zydus Lifesciences Limited
Category: prescription | Type: HUMAN PRESCRIPTION DRUG LABEL
Date: 20251222

ACTIVE INGREDIENTS: MICAFUNGIN SODIUM 10 mg/1 mL
INACTIVE INGREDIENTS: LACTOSE MONOHYDRATE; ANHYDROUS CITRIC ACID; SODIUM HYDROXIDE

Micafungin for Injection, for intravenous use

PACKAGE LABEL.PRINCIPAL DISPLAY PANEL

NDC 70771-1683-6

Micafungin for Injection

50 mg/vial

For Intravenous Infusion Only

10 x 50 mg Single-Dose Vials

Rx only

NDC 70771-1684-6

Micafungin for Injection

100 mg/vial

For Intravenous Infusion Only

10 x 100 mg Single-Dose Vials

Rx only